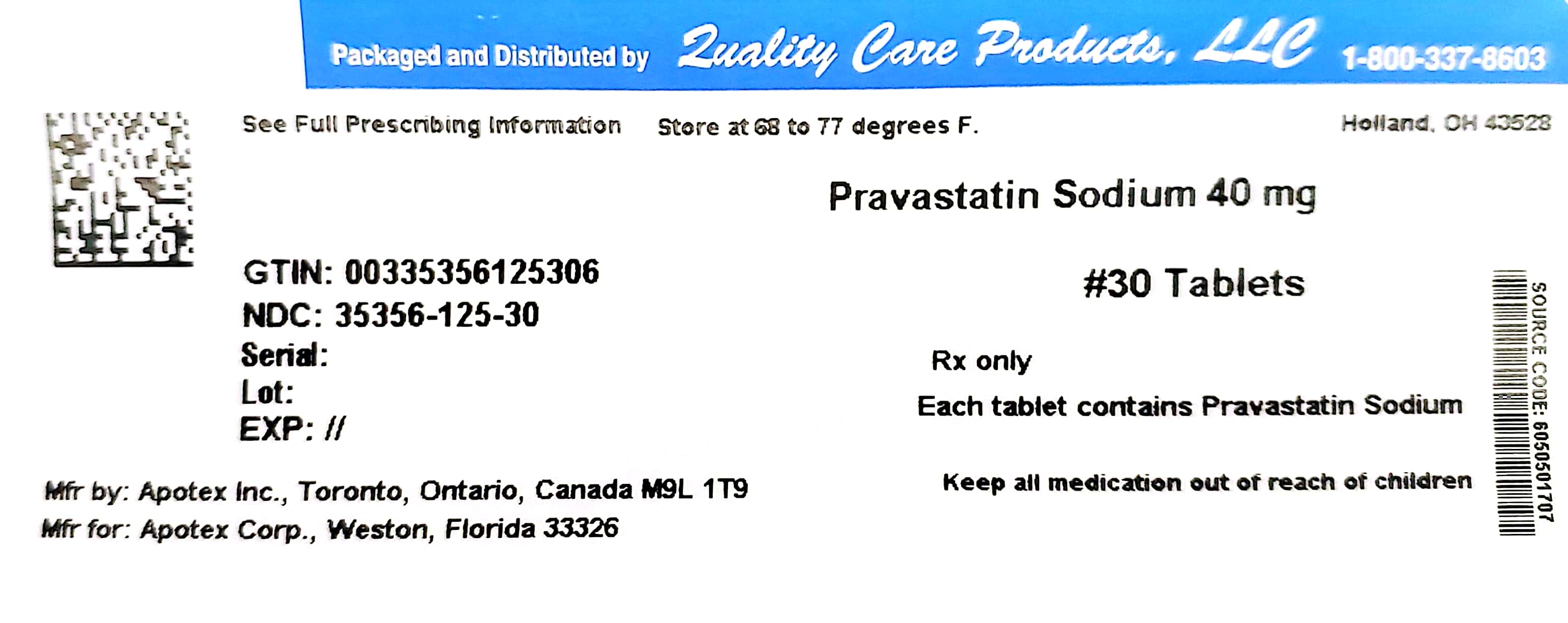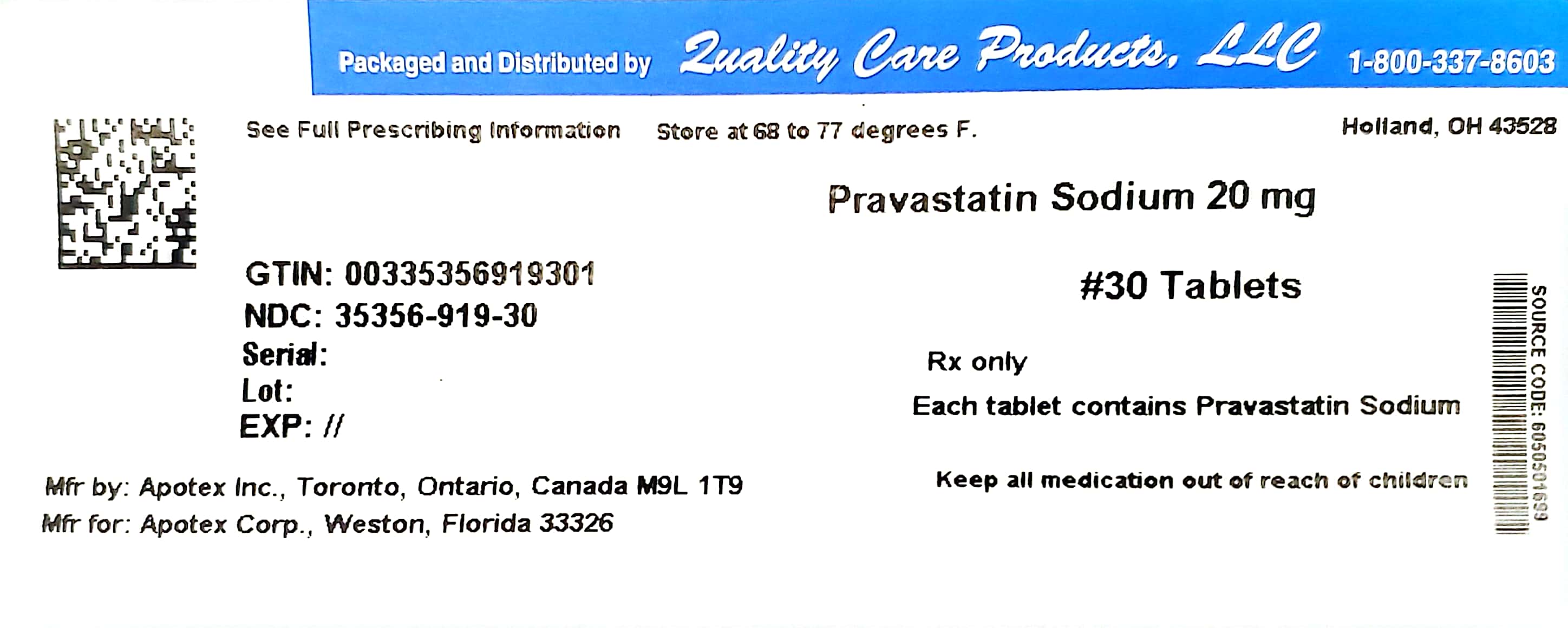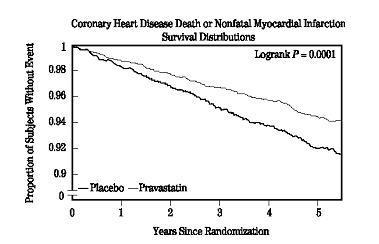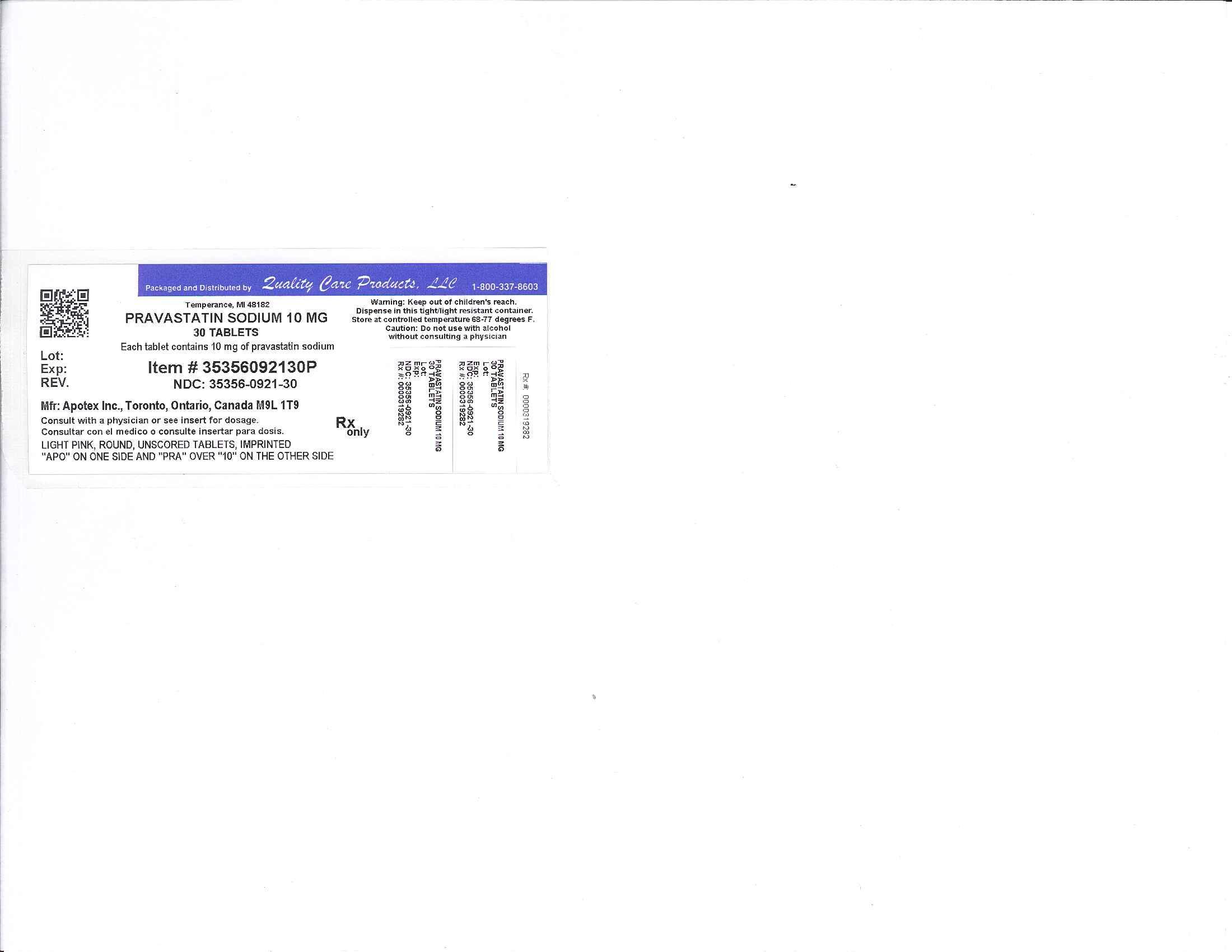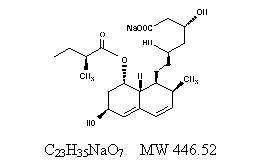 DRUG LABEL: Pravastatin Sodium
NDC: 35356-921 | Form: TABLET
Manufacturer: Lake Erie Medical DBA Quality Care Products LLC
Category: prescription | Type: HUMAN PRESCRIPTION DRUG LABEL
Date: 20241211

ACTIVE INGREDIENTS: pravastatin sodium 10 mg/1 1
INACTIVE INGREDIENTS: croscarmellose sodium; lactose monohydrate; magnesium stearate; cellulose, microcrystalline; Ferric Oxide Red

Pravastatin Sodium Tablets, USP
10 mg, 20 mg, 40 mg and 80 mg

DESCRIPTION

Pravastatin sodium is one of a class of lipid-lowering compounds, the HMG-CoA reductase inhibitors, which reduce cholesterol biosynthesis. These agents are competitive inhibitors of 3-hydroxy-3-methylglutaryl-coenzyme A (HMG-CoA) reductase, the enzyme catalyzing the early rate-limiting step in cholesterol biosynthesis, conversion of HMG-CoA to mevalonate.

Pravastatin sodium is designated chemically as Sodium (3R,5R)-3,5-dihydroxy-7-[(1S,2S,6S,8S,8aR)-6-hydroxy-2-methyl-8-[[(2S)-methylbutanoyl]oxy]-1,2,6,7,8,8a-hexahydronaphthalen-1-yl]heptanoate.

Structural formula:

Pravastatin sodium is an odorless, white to off-white, fine or crystalline powder. It is a relatively polar hydrophilic compound with a partition coefficient (octanol/water) of 0.59 at a pH of 7.0. It is soluble in methanol and water (>300 mg/mL), slightly soluble in isopropanol, and practically insoluble in acetone, acetonitrile, chloroform, and ether.

Each tablet, for oral administration contains 10 mg, 20 mg, 40 mg or 80 mg of pravastatin sodium. In addition, each tablet contains the following inactive ingredients: croscarmellose sodium, lactose monohydrate, magnesium stearate and microcrystalline cellulose. The 10 mg tablet also contains red ferric oxide, the 20 mg tablet also contains yellow ferric oxide, and the 40 mg tablet also contains a blend of yellow ferric oxide and FD&C blue #1, and the 80 mg tablet also contains yellow ferric oxide.

CLINICAL PHARMACOLOGY

Cholesterol and triglycerides in the bloodstream circulate as part of lipoprotein complexes. These complexes can be separated by density ultracentrifugation into high (HDL), intermediate (IDL), low (LDL), and very low (VLDL) density lipoprotein fractions. Triglycerides (TG) and cholesterol synthesized in the liver are incorporated into very low density lipoproteins (VLDLs) and released into the plasma for delivery to peripheral tissues. In a series of subsequent steps, VLDLs are transformed into intermediate density lipoproteins (IDLs), and cholesterol-rich low density lipoproteins (LDLs). High density lipoproteins (HDLs), containing apolipoprotein A, are hypothesized to participate in the reverse transport of cholesterol from tissues back to the liver.

Pravastatin sodium produces its lipid-lowering effect in two ways. First, as a consequence of its reversible inhibition of HMG-CoA reductase activity, it effects modest reductions in intracellular pools of cholesterol. This results in an increase in the number of LDL-receptors on cell surfaces and enhanced receptor-mediated catabolism and clearance of circulating LDL. Second, pravastatin inhibits LDL production by inhibiting hepatic synthesis of VLDL, the LDL precursor.

Clinical and pathologic studies have shown that elevated levels of total cholesterol (Total-C), low density lipoprotein cholesterol (LDL-C), and apolipoprotein B (ApoB – a membrane transport complex for LDL) promote human atherosclerosis. Similarly, decreased levels of HDL-cholesterol (HDL-C) and its transport complex, apolipoprotein A, are associated with the development of atherosclerosis. Epidemiologic investigations have established that cardiovascular morbidity and mortality vary directly with the level of Total-C and LDL-C and inversely with the level of HDL-C. Like LDL, cholesterol-enriched triglyceride-rich lipoproteins, including VLDL, IDL, and remnants, can also promote atherosclerosis. Elevated plasma TG are frequently found in a triad with low HDL-C levels and small LDL particles, as well as in association with non-lipid metabolic risk factors for coronary heart disease. As such, total plasma TG has not consistently been shown to be an independent risk factor for CHD. Furthermore, the independent effect of raising HDL or lowering TG on the risk of coronary and cardiovascular morbidity and mortality has not been determined. In both normal volunteers and patients with hypercholesterolemia, treatment with pravastatin sodium reduced Total-C, LDL-C, and apolipoprotein B. pravastatin sodium also reduced VLDL-C and TG and produced increases in HDL-C and apolipoprotein A. The effects of pravastatin on Lp (a), fibrinogen, and certain other independent biochemical risk markers for coronary heart disease are unknown. Although pravastatin is relatively more hydrophilic than other HMG-CoA reductase inhibitors, the effect of relative hydrophilicity, if any, on either efficacy or safety has not been established.

In one primary (West of Scotland Coronary Prevention Study - WOS)^1 and pravastatin sodium has been shown to reduce cardiovascular morbidity and mortality across a wide range of cholesterol levels (see Clinical Studies).

Pharmacokinetics/Metabolism

Pravastatin sodium is administered orally in the active form. In clinical pharmacology studies in man, pravastatin is rapidly absorbed, with peak plasma levels of parent compound attained 1 to 1.5 hours following ingestion. Based on urinary recovery of radiolabeled drug, the average oral absorption of pravastatin is 34% and absolute bioavailability is 17%. While the presence of food in the gastrointestinal tract reduces systemic bioavailability, the lipid-lowering effects of the drug are similar whether taken with, or 1 hour prior to, meals.

Pravastatin undergoes extensive first-pass extraction in the liver (extraction ratio 0.66), which is its primary site of action, and the primary site of cholesterol synthesis and of LDL-C clearance. In vitro studies demonstrated that pravastatin is transported into hepatocytes with substantially less uptake into other cells. In view of pravastatin's apparently extensive first-pass hepatic metabolism, plasma levels may not necessarily correlate perfectly with lipid-lowering efficacy. Pravastatin plasma concentrations [including: area under the concentration-time curve (AUC), peak (Cmax), and steady-state minimum (Cmin)] are directly proportional to administered dose. Systemic bioavailability of pravastatin administered following a bedtime dose was decreased 60% compared to that following an AM dose. Despite this decrease in systemic bioavailability, the efficacy of pravastatin administered once daily in the evening, although not statistically significant, was marginally more effective than that after a morning dose. This finding of lower systemic bioavailability suggests greater hepatic extraction of the drug following the evening dose. Steady-state AUCs, Cmax and Cmin plasma concentrations showed no evidence of pravastatin accumulation following once or twice daily administration of pravastatin sodium tablets. Approximately 50% of the circulating drug is bound to plasma proteins. Following single dose administration of ^14C-pravastatin, the elimination half-life (t½) for total radioactivity (pravastatin plus metabolites) in humans is 77 hours.

Pravastatin sodium, like other HMG-CoA reductase inhibitors, has variable bioavailability. The coefficient of variation (CV), based on between-subject variability, was 50% to 60% for AUC. Pravastatin 20 mg was administered under fasting conditions in adults. The geometric means of Cmax and AUC ranged from 23.3 to 26.3 ng/mL and from 54.7 to 62.2 ng x hr/mL, respectively.

Approximately 20% of a radiolabeled oral dose is excreted in urine and 70% in the feces. After intravenous administration of radiolabeled pravastatin to normal volunteers, approximately 47% of total body clearance was via renal excretion and 53% by non-renal routes (i.e., biliary excretion and biotransformation). Since there are dual routes of elimination, the potential exists both for compensatory excretion by the alternate route as well as for accumulation of drug and/or metabolites in patients with renal or hepatic insufficiency.

In a study comparing the kinetics of pravastatin in patients with biopsy confirmed cirrhosis (N=7) and normal subjects (N=7), the mean AUC varied 18-fold in cirrhotic patients and 5-fold in healthy subjects. Similarly, the peak pravastatin values varied 47-fold for cirrhotic patients compared to 6-fold for healthy subjects.

Biotransformation pathways elucidated for pravastatin include: (a) isomerization to 6-epi pravastatin and the 3α-hydroxyisomer of pravastatin (SQ 31,906), (b) enzymatic ring hydroxylation to SQ 31,945, (c) ω-1 oxidation of the ester side chain, (d) β-oxidation of the carboxy side chain, (e) ring oxidation followed by aromatization, (f) oxidation of a hydroxyl group to a keto group, and (g) conjugation. The major degradation product is the 3α-hydroxy isomeric metabolite, which has one-tenth to one-fortieth the HMG-CoA reductase inhibitory activity of the parent compound.

In a single oral dose study using pravastatin 20 mg, the mean AUC for pravastatin was approximately 27% greater and the mean cumulative urinary excretion (CUE) approximately 19% lower in elderly men (65 to 75 years old) compared with younger men (19 to 31 years old). In a similar study conducted in women, the mean AUC for pravastatin was approximately 46% higher and the mean CUE approximately 18% lower in elderly women (65 to 78 years old) compared with younger women (18 to 38 years old). In both studies, Cmax, Tmax and t½ values were similar in older and younger subjects.

After 2 weeks of once-daily 20 mg oral pravastatin administration, the geometric means of AUC were 80.7 (CV 44%) and 44.8 (CV 89%) ng*hr/mL for children (8-11 years, N=14) and adolescents (12-16 years, N=10), respectively. The corresponding values for Cmax were 42.4 (CV 54%) and 18.6 ng/mL (CV 100%) for children and adolescents, respectively. No conclusion can be made based on these findings due to the small number of samples and large variability.

Clinical Studies

Prevention of Coronary Heart Disease

In the Pravastatin Primary Prevention Study (West of Scotland Coronary Prevention Study – WOS)^1, the effect of pravastatin sodium on fatal and nonfatal coronary heart disease (CHD) was assessed in 6595 men 45–64 years of age, without a previous myocardial infarction (MI), and with LDL-C levels between 156–254 mg/dL (4–6.7 mmol/L). In this randomized, double-blind, placebo-controlled study, patients were treated with standard care, including dietary advice, and either pravastatin 40 mg daily (N=3302) or placebo (N=3293) and followed for a median duration of 4.8 years. Median (25th, 75th percentile) percent changes from baseline after 6 months of pravastatin treatment in Total-C, LDL-C, TG, and HDL-C were -20.3 (-26.9, -11.7), -27.7 (-36.0, -16.9), -9.1 (-27.6, 12.5), and 6.7 (-2.1, 15.6), respectively.

Pravastatin sodium significantly reduced the rate of first coronary events (either coronary heart disease [CHD] death or nonfatal MI) by 31% [248 events in the placebo group (CHD death=44, nonfatal MI=204) vs 174 events in the pravastatin sodium group (CHD death=31, nonfatal MI=143), p=0.0001 (see figure below)]. The risk reduction with pravastatin sodium was similar and significant throughout the entire range of baseline LDL cholesterol levels. This reduction was also similar and significant across the age range studied with a 40% risk reduction for patients younger than 55 years and a 27% risk reduction for patients 55 years and older. The Pravastatin Primary Prevention Study included only men, and therefore it is not clear to what extent these data can be extrapolated to a similar population of female patients.

Pravastatin sodium also significantly decreased the risk for undergoing myocardial revascularization procedures (coronary artery bypass graft [CABG] surgery or percutaneous transluminal coronary angioplasty [PTCA]) by 37% (80 vs 51 patients, p=0.009) and coronary angiography by 31% (128 vs 90, p=0.007). Cardiovascular deaths were decreased by 32% (73 vs 50, p=0.03) and there was no increase in death from non-cardiovascular causes.

Secondary Prevention of Cardiovascular Events

In the Pravastatin Limitation of Atherosclerosis in the Coronary Arteries (PLAC I)^2 study, the effect of pravastatin therapy on coronary atherosclerosis was assessed by coronary angiography in patients with coronary disease and moderate hypercholesterolemia (baseline LDL-C range: 130-190 mg/dL). In this double-blind, multicenter, controlled clinical trial, angiograms were evaluated at baseline and at three years in 264 patients. Although the difference between pravastatin and placebo for the primary endpoint (per-patient change in mean coronary artery diameter) and one of two secondary endpoints (change in percent lumen diameter stenosis) did not reach statistical significance, for the secondary endpoint of change in minimum lumen diameter, statistically significant slowing of disease was seen in the pravastatin treatment group (p=0.02).

In the Regression Growth Evaluation Statin Study (REGRESS)^3, the effect of pravastatin on coronary atherosclerosis was assessed by coronary angiography in 885 patients with angina pectoris, angiographically documented coronary artery disease and hypercholesterolemia (baseline total cholesterol range: 160-310 mg/dL). In this double-blind, multicenter, controlled clinical trial, angiograms were evaluated at baseline and at two years in 653 patients (323 treated with pravastatin). Progression of coronary atherosclerosis was significantly slowed in the pravastatin group as assessed by changes in mean segment diameter (p=0.037) and minimum obstruction diameter (p=0.001).

Analysis of pooled events from PLAC I, the Pravastatin, Lipids and Atherosclerosis in the Carotids Study (PLAC II)^4, REGRESS, and the Kuopio Atherosclerosis Prevention Study (KAPS)^5 (combined N=1891) showed that treatment with pravastatin was associated with a statistically significant reduction in the composite event rate of fatal and nonfatal myocardial infarction (46 events or 6.4% for placebo versus 21 events or 2.4% for pravastatin, p=0.001). The predominant effect of pravastatin was to reduce the rate of nonfatal myocardial infarction.

Primary Hypercholesterolemia (Fredrickson Type IIa and IIb)

Pravastatin sodium is highly effective in reducing Total-C, LDL-C and Triglycerides (TG) in patients with heterozygous familial, presumed familial combined and non-familial (non-FH) forms of primary hypercholesterolemia, and mixed dyslipidemia. A therapeutic response is seen within 1 week, and the maximum response usually is achieved within 4 weeks. This response is maintained during extended periods of therapy. In addition, pravastatin sodium is effective in reducing the risk of acute coronary events in hypercholesterolemic patients with and without previous myocardial infarction.

A single daily dose is as effective as the same total daily dose given twice a day. In multicenter, double-blind, placebo-controlled studies of patients with primary hypercholesterolemia, treatment with pravastatin in daily doses ranging from 10 mg to 40 mg consistently and significantly decreased Total-C, LDL-C, TG, and Total-C/HDL-C and LDL-C/HDL-C ratios (see Table 1).

In a pooled analysis of two multicenter, double-blind, placebo-controlled studies of patients with primary hypercholesterolemia, treatment with pravastatin at a daily dose of 80 mg (N=277) significantly decreased Total-C, LDL-C, and TG. The 25th and 75th percentile changes from baseline in LDL-C for pravastatin 80 mg were -43% and -30%. The efficacy results of the individual studies were consistent with the pooled data (see Table 1).

Treatment with pravastatin sodium modestly decreased VLDL-C and pravastatin sodium across all doses produced variable increases in HDL-C (see Table 1).

Table 1: LIPID - Primary and Secondary Endpoints
 | Number (%) of Subjects
Event | Pravastatin 40 mg (N=4512) | Placebo (N=4502) | Risk Reduction | P-value
Primary Endpoint
CHD mortality | 287 (6.4) | 373 (8.3) | 24% | 0.0004
Secondary Endpoints
Total mortality | 498 (11.0) | 633 (14.1) | 23% | <0.0001
CHD mortality or nonfatal MI | 557 (12.3) | 715 (15.9) | 24% | <0.0001
Myocardial revascularization procedures (CABG or PTCA) | 584 (12.9) | 706 (15.7) | 20% | <0.0001
Stroke
All-cause | 169 (3.7) | 204 (4.5) | 19% | 0.0477
Non-hemorrhagic | 154 (3.4) | 196 (4.4) | 23% | 0.0154
Cardiovascular mortality | 331 (7.3) | 433 (9.6) | 25% | <0.0001

In another clinical trial, patients treated with pravastatin in combination with cholestyramine (70% of patients were taking cholestyramine 20 or 24 g per day) had reductions equal to or greater than 50% in LDL-C. Furthermore, pravastatin attenuated cholestyramine-induced increases in TG levels (which are themselves of uncertain clinical significance).

Hypertriglyceridemia (Fredrickson Type IV)

The response to pravastatin in patients with Type IV hyperlipidemia (baseline TG >200 mg/dL and LDL-C <160 mg/dL) was evaluated in a subset of 429 patients. For pravastatin-treated subjects, the median (min, max) baseline triglyceride level was 246.0 (200.5, 349.5) mg/dL. (See Table 2.)

Table 2: Patients with Fredrickson Type IV Hyperlipidemia Median (25th, 75th percentile) Percent Change from Baseline
 | Pravastatin 40 mg (N=429) | Placebo (N=430)
Triglycerides | -21.1 (-34.8, 1.3) | -6.3 (-23.1, 18.3)
Total-C | -22.1 (-27.1, -14.8) | 0.2 (-6.9, 6.8)
LDL-C | -31.7 (-39.6, -21.5) | 0.7 (-9.0, 10.0)
HDL-C | 7.4 (-1.2, 17.7) | 2.8 (-5.7, 11.7)
Non-HDL-C | -27.2 (-34.0, -18.5) | -0.8 (-8.2, 7.0)

Dysbetalipoproteinemia (Fredrickson Type III)

The response to pravastatin in two double-blind crossover studies of 46 patients with genotype E2/E2 and Fredrickson Type III dysbetalipoproteinemia is shown in Table 3.

Table 3: Patients with Fredrickson Type III Dysbetalipoproteinemia Median (min, max) Percent Change from Baseline
 | Median (min, max) at Baseline (mg/dL) | Median % Change (min, max) Pravastatin 40 mg (N=20)
Study 1
Total-C | 386.5 (245.0, 672.0) | -32.7 (-58.5, 4.6)
Triglycerides | 443.0 (275.0, 1299.0) | -23.7 (-68.5, 44.7)
VLDL-C* | 206.5 (110.0, 379.0) | -43.8 (-73.1, -14.3)
LDL-C* | 117.5 (80.0, 170.0) | -40.8 (-63.7, 4.6)
HDL-C | 30.0 (18.0, 88.0) | 6.4 (-45.0, 105.6)
Non-HDL-C | 344.5 (215.0, 646.0) | -36.7 (-66.3, 5.8)
*N=14
 | Median (min, max) at Baseline (mg/dL) | Median % Change (min, max) Pravastatin 40 mg (N=26)
Study 2
Total-C | 340.3 (230.1, 448.6) | -31.4 (-54.5, -13.0)
Triglycerides | 343.2 (212.6, 845.9) | -11.9 (-56.5, 44.8)
VLDL-C | 145.0 (71.5, 309.4) | -35.7 (-74.7, 19.1)
LDL-C | 128.6 (63.8, 177.9) | -30.3 (-52.2, 13.5)
HDL-C | 38.7 (27.1, 58.0) | 5.0 (-17.7, 66.7)
Non-HDL-C | 295.8 (195.3, 421.5) | -35.5 (-81.0, -13.5)

Pediatric Clinical Study

A double-blind, placebo-controlled study in 214 patients (100 boys and 114 girls) with heterozygous familial hypercholesterolemia (HeFH), aged 8-18 years was conducted for two (2) years. The children (aged 8-13 years) were randomized to placebo (N=63) or 20 mg of pravastatin daily (N=65) and the adolescents (aged 14-18 years) were randomized to placebo (N=45) or 40 mg of pravastatin daily (N=41). Inclusion in the study required an LDL-C level >95th percentile for age and sex and one parent with either a clinical or molecular diagnosis of familial hypercholesterolemia. The mean baseline LDL-C value was 239 mg/dL and 237 mg/dL in the pravastatin (range: 151-405 mg/dL) and placebo (range: 154-375 mg/dL) groups, respectively.

Pravastatin significantly decreased plasma levels of LDL-C, Total-C, and apolipoprotein B in both children and adolescents (see Table 4). The effect of pravastatin treatment in the two age groups was similar.

Table 4: Lipid-Lowering Effects of Pravastatin in Pediatric Patients with Heterozygous Familial Hypercholesterolemia: Least-Squares Mean Percent Change from Baseline at Month 24 (Last Observation Carried Forward: Intent-to-Treat)*
 | Pravastatin 20 mg (Aged 8-13 years) N=65 | Pravastatin 40 mg (Aged 14-18 years) N=41 | Combined Pravastatin (Aged 8-18 years) N=106 | Combined Placebo (Aged 8-18 years) N=108 | 95% CI of the Difference Between Combined Pravastatin and Placebo
LDL-C | -26.04** | -21.07** | -24.07** | -1.52 | (-26.74, -18.86)
TC | -20.75** | -13.08** | -17.72** | -0.65 | (-20.40, -13.83)
HDL-C | 1.04 | 13.71 | 5.97 | 3.13 | (-1.71, 7.43)
TG | -9.58 | -0.30 | -5.88 | -3.27 | (-13.95, 10.01)
ApoB (N) | -23.16** (61) | -18.08** (39) | -21.11** (100) | -0.97 (106) | (-24.29, -16.18)
* The above least-squares mean values were calculated based on log-transformed lipid values.
** Significant at p≤0.0001 when compared with placebo

The mean achieved LDL-C was 186 mg/dL (range: 67-363 mg/dL) in the pravastatin group compared to 236 mg/dL (range: 105-438 mg/dL) in the placebo group.

The safety and efficacy of pravastatin doses above 40 mg daily have not been studied in children. The long-term efficacy of pravastatin therapy in childhood to reduce morbidity and mortality in adulthood has not been established.

INDICATIONS AND USAGE

Therapy with Pravastatin Sodium Tablets, USP should be considered in those individuals at increased risk for atherosclerosis-related clinical events as a function of cholesterol level, the presence or absence of coronary heart disease, and other risk factors.

Primary Prevention of Coronary Events

In hypercholesterolemic patients without clinically evident coronary heart disease, Pravastatin Sodium Tablets, USP are indicated to:

- Reduce the risk of myocardial infarction
- Reduce the risk of undergoing myocardial revascularization procedures
- Reduce the risk of cardiovascular mortality with no increase in death from non-cardiovascular causes.

Hyperlipidemia

Pravastatin Sodium Tablets, USP are indicated as an adjunct to diet to reduce elevated Total-C, LDL-C, ApoB, and TG levels and to increase HDL-C in patients with primary hypercholesterolemia and mixed dyslipidemia (Fredrickson Type IIa and IIb).^8

Pravastatin Sodium Tablets, USP are indicated as adjunctive therapy to diet for the treatment of patients with elevated serum triglyceride levels (Fredrickson Type IV).

Pravastatin Sodium Tablets, USP are indicated for the treatment of patients with primary dysbetalipoproteinemia (Fredrickson Type III) who do not respond adequately to diet.

Pravastatin Sodium Tablets, USP are indicated as an adjunct to diet and lifestyle modification for treatment of HeFH in children and adolescent patients ages 8 years and older if after an adequate trial of diet the following findings are present:

1. LDL-C remains ≥190 mg/dL or
2. LDL-C remains ≥160 mg/dL and:
  - there is a positive family history of premature cardiovascular disease or
  - two or more other CVD risk factors are present in the patient.

Lipid-altering agents should be used in addition to a diet restricted in saturated fat and cholesterol when the response to diet and other nonpharmacological measures alone has been inadequate (see NCEP Guidelines below).

Prior to initiating therapy with pravastatin, secondary causes for hypercholesterolemia (e.g., poorly controlled diabetes mellitus, hypothyroidism, nephrotic syndrome, dysproteinemias, obstructive liver disease, other drug therapy, alcoholism) should be excluded, and a lipid profile performed to measure Total-C, HDL-C, and TG. For patients with triglycerides (TG) <400 mg/dL (<4.5 mmol/L), LDL-C can be estimated using the following equation:

LDL-C = Total-C - HDL-C - ^1/5 TG

For TG levels >400 mg/dL (>4.5 mmol/L), this equation is less accurate and LDL-C concentrations should be determined by ultracentrifugation. In many hypertriglyceridemic patients, LDL-C may be low or normal despite elevated Total-C. In such cases, HMG-CoA reductase inhibitors are not indicated.

Lipid determinations should be performed at intervals of no less than four weeks and dosage adjusted according to the patient's response to therapy.

The National Cholesterol Education Program's Treatment Guidelines are summarized below:

Table 5: NCEP Treatment Guidelines: LDL-C Goals and Cutpoints for Therapeutic Lifestyle Changes and Drug Therapy in Different Risk Categories
Risk Category | LDL Goal (mg/dL) | LDL Level at Which to Initiate Therapeutic Lifestyle Changes (mg/dL) | LDL Level at Which to Consider Drug Therapy (mg/dL)
CHDa or CHD risk equivalents (10-year risk >20%) | <100 | ≥100 | ≥130 (100-129: drug optional)b
2+ Risk factors (10-year risk ≤20 %) | <130 | ≥130 | 10-year risk 10%-20%: ≥130
2+ Risk factors (10-year risk ≤20 %) | <130 | ≥130 | 10-year risk <10%: ≥160
0-1 Risk factorc | <160 | ≥160 | ≥190 (160-189: LDL-lowering drug optional)
a CHD, coronary heart disease.
b Some authorities recommend use of LDL-lowering drugs in this category if an LDL-C level of <100 mg/dL cannot be achieved by therapeutic lifestyle changes. Others prefer use of drugs that primarily modify triglycerides and HDL-C, e.g., nicotinic acid or fibrate. Clinical judgement also may call for deferring drug therapy in this subcategory.
c Almost all people with 0-1 risk factor have 10-year risk <10%; thus, 10-year risk assessment in people with 0-1 risk factor is not necessary.

After the LDL-C goal has been achieved, if the TG is still ≥200 mg/dL, non-HDL-C (Total-C minus HDL-C) becomes a secondary target of therapy. Non-HDL-C goals are set 30 mg/dL higher than LDL-C goals for each risk category.

At the time of hospitalization for an acute coronary event, consideration can be given to initiating drug therapy at discharge if the LDL-C is ≥130 mg/dL (see NCEP Guidelines, above).

Since the goal of treatment is to lower LDL-C, the NCEP recommends that LDL-C levels be used to initiate and assess treatment response. Only if LDL-C levels are not available, should the Total-C be used to monitor therapy.

As with other lipid-lowering therapy, pravastatin sodium tablets are not indicated when hypercholesterolemia is due to hyperalphalipoproteinemia (elevated HDL-C).

The NCEP classification of cholesterol levels in pediatric patients with a familial history of hypercholesterolemia or premature cardiovascular disease is summarized below:

Category | Total-C (mg/dL) | LDL-C (mg/dL)
Acceptable | <170 | <110
Borderline | 170-199 | 110-129
High | ≥200 | ≥130

CONTRAINDICATIONS

Hypersensitivity to any component of this medication.

Active liver disease or unexplained, persistent elevations of serum transaminases (see WARNINGS).

Pregnancy and Lactation. Atherosclerosis is a chronic process and discontinuation of lipid-lowering drugs during pregnancy should have little impact on the outcome of long-term therapy of primary hypercholesterolemia. Cholesterol and other products of cholesterol biosynthesis are essential components for fetal development (including synthesis of steroids and cell membranes). Since HMG-CoA reductase inhibitors decrease cholesterol synthesis and possibly the synthesis of other biologically active substances derived from cholesterol, they are contraindicated during pregnancy and in nursing mothers. Pravastatin should be administered to women of childbearing age only when such patients are highly unlikely to conceive and have been informed of the potential hazards. If the patient becomes pregnant while taking this class of drug, therapy should be discontinued immediately and the patient apprised of the potential hazard to the fetus (see PRECAUTIONS: Pregnancy).

WARNINGS

Liver Enzymes

HMG-CoA reductase inhibitors, like some other lipid-lowering therapies, have been associated with biochemical abnormalities of liver function. In placebo-controlled clinical trials (see CLINICAL PHARMACOLOGY: Clinical Studies), subjects were exposed to pravastatin or placebo. In an analysis of serum transaminase values (ALT, AST), incidences of marked abnormalities were compared between the pravastatin and placebo treatment groups; a marked abnormality was defined as a post-treatment test value greater than three times the upper limit of normal for subjects with pretreatment values less than or equal to the upper limit of normal, or four times the pretreatment value for subjects with pretreatment values greater than the upper limit of normal but less than 1.5 times the upper limit of normal. Marked abnormalities of ALT or AST occurred with similar low frequency (≤1.2%) in both treatment groups. Overall, clinical trial experience showed that liver function test abnormalities observed during pravastatin therapy were usually asymptomatic, not associated with cholestasis, and did not appear to be related to treatment duration. In a 320-patient placebo-controlled clinical trial, subjects with chronic (>6 months) stable liver disease, due primarily to hepatitis C or non-alcoholic fatty liver disease, were treated with 80 mg pravastatin or placebo for up to 9 months. The primary safety endpoint was the proportion of subjects with at least one ALT ≥2 times the upper limit of normal for those with normal ALT (≤ the upper limit of normal) at baseline or a doubling of the baseline ALT for those with elevated ALT (> the upper limit of normal) at baseline. By Week 36, 12 out of 160 (7.5%) subjects treated with pravastatin met the prespecified safety ALT endpoint compared to 20 out of 160 (12.5%) subjects receiving placebo. Conclusions regarding liver safety are limited since the study was not large enough to establish similarity between groups (with 95% confidence) in the rates of ALT elevation.

It is recommended that liver function tests be performed prior to the initiation of therapy, prior to the elevation of the dose, and when otherwise clinically indicated.

Active liver disease or unexplained persistent transaminase elevations are contraindications to the use of pravastatin (see CONTRAINDICATIONS). Caution should be exercised when pravastatin is administered to patients who have a recent history of liver disease, have signs that may suggest liver disease (e.g., unexplained aminotransferase elevations, jaundice), or are heavy users of alcohol (see CLINICAL PHARMACOLOGY: Pharmacokinetics/Metabolism). Such patients should be closely monitored, started at the lower end of the recommended dosing range, and titrated to the desired therapeutic effect.

Patients who develop increased transaminase levels or signs and symptoms of liver disease should be monitored with a second liver function evaluation to confirm the finding and be followed thereafter with frequent liver function tests until the abnormality(ies) return to normal. Should an increase in AST or ALT of three times the upper limit of normal or greater persist, withdrawal of pravastatin therapy is recommended.

Skeletal Muscle

Rare cases of rhabdomyolysis with acute renal failure secondary to myoglobinuria have been reported with pravastatin and other drugs in this class. Uncomplicated myalgia has also been reported in pravastatin-treated patients (see ADVERSE REACTIONS). Myopathy, defined as muscle aching or muscle weakness in conjunction with increases in creatine phosphokinase (CPK) values to greater than 10 times the upper limit of normal, was rare (<0.1%) in pravastatin clinical trials. Myopathy should be considered in any patient with diffuse myalgias, muscle tenderness or weakness, and/or marked elevation of CPK. Patients should be advised to report promptly unexplained muscle pain, tenderness or weakness, particularly if accompanied by malaise or fever. Pravastatin therapy should be discontinued if markedly elevated CPK levels occur or myopathy is diagnosed or suspected. Pravastatin therapy should also be temporarily withheld in any patient experiencing an acute or serious condition predisposing to the development of renal failure secondary to rhabdomyolysis, e.g., sepsis; hypotension; major surgery; trauma; severe metabolic, endocrine, or electrolyte disorders; or uncontrolled epilepsy.

The risk of myopathy during treatment with another HMG-CoA reductase inhibitor is increased with concurrent therapy with either erythromycin, cyclosporine, niacin, or fibrates. However, neither myopathy nor significant increases in CPK levels have been observed in three reports involving a total of 100 post-transplant patients (24 renal and 76 cardiac) treated for up to two years concurrently with pravastatin 10-40 mg and cyclosporine. Some of these patients also received other concomitant immunosuppressive therapies. Further, in clinical trials involving small numbers of patients who were treated concurrently with pravastatin and niacin, there were no reports of myopathy. Also, myopathy was not reported in a trial of combination pravastatin (40 mg/day) and gemfibrozil (1200 mg/day), although 4 of 75 patients on the combination showed marked CPK elevations versus one of 73 patients receiving placebo. There was a trend toward more frequent CPK elevations and patient withdrawals due to musculoskeletal symptoms in the group receiving combined treatment as compared with the groups receiving placebo, gemfibrozil, or pravastatin monotherapy (see PRECAUTIONS: Drug Interactions). The use of fibrates alone may occasionally be associated with myopathy. The combined use of pravastatin and fibrates should be avoided unless the benefit of further alterations in lipid levels is likely to outweigh the increased risk of this drug combination.

PRECAUTIONS

General

Pravastatin sodium may elevate creatine phosphokinase and transaminase levels (see ADVERSE REACTIONS). This should be considered in the differential diagnosis of chest pain in a patient on therapy with pravastatin.

Homozygous Familial Hypercholesterolemia. Pravastatin has not been evaluated in patients with rare homozygous familial hypercholesterolemia. In this group of patients, it has been reported that HMG-CoA reductase inhibitors are less effective because the patients lack functional LDL receptors.

Renal Insufficiency. A single 20 mg oral dose of pravastatin was administered to 24 patients with varying degrees of renal impairment (as determined by creatinine clearance). No effect was observed on the pharmacokinetics of pravastatin or its 3α-hydroxy isomeric metabolite (SQ 31,906). A small increase was seen in mean AUC values and half-life (t½) for the inactive enzymatic ring hydroxylation metabolite (SQ 31,945). Given this small sample size, the dosage administered, and the degree of individual variability, patients with renal impairment who are receiving pravastatin should be closely monitored.

Information for Patients

Patients should be advised to report promptly unexplained muscle pain, tenderness or weakness, particularly if accompanied by malaise or fever (see WARNINGS: Skeletal Muscle).

Drug Interactions

Immunosuppressive Drugs, Gemfibrozil, Niacin (Nicotinic Acid), Erythromycin: See WARNINGS: Skeletal Muscle.

Cytochrome P450 3A4 Inhibitors: In vitro and in vivo data indicate that pravastatin is not metabolized by cytochrome P450 3A4 to a clinically significant extent. This has been shown in studies with known cytochrome P450 3A4 inhibitors (see Diltiazem and Itraconazole below). Other examples of cytochrome P450 3A4 inhibitors include ketoconazole, mibefradil, and erythromycin.

Diltiazem: Steady-state levels of diltiazem (a known, weak inhibitor of P450 3A4) had no effect on the pharmacokinetics of pravastatin. In this study, the AUC and Cmax of another HMG-CoA reductase inhibitor which is known to be metabolized by cytochrome P450 3A4 increased by factors of 3.6 and 4.3, respectively.

Itraconazole: The mean AUC and Cmax for pravastatin were increased by factors of 1.7 and 2.5, respectively, when given with itraconazole (a potent P450 3A4 inhibitor which also inhibits p-glycoprotein transport) as compared to placebo. The mean t½ was not affected by itraconazole, suggesting that the relatively small increases in Cmax and AUC were due solely to increased bioavailability rather than a decrease in clearance, consistent with inhibition of p-glycoprotein transport by itraconazole. This drug transport system is thought to affect bioavailability and excretion of HMG-CoA reductase inhibitors, including pravastatin. The AUC and Cmax of another HMG-CoA reductase inhibitor which is known to be metabolized by cytochrome P450 3A4 increased by factors of 19 and 17, respectively, when given with itraconazole.

Antipyrine: Since concomitant administration of pravastatin had no effect on the clearance of antipyrine, interactions with other drugs metabolized via the same hepatic cytochrome isozymes are not expected.

Cholestyramine/Colestipol: Concomitant administration resulted in an approximately 40 to 50% decrease in the mean AUC of pravastatin. However, when pravastatin was administered 1 hour before or 4 hours after cholestyramine or 1 hour before colestipol and a standard meal, there was no clinically significant decrease in bioavailability or therapeutic effect. (See DOSAGE AND ADMINISTRATION: Concomitant Therapy.)

Warfarin: Concomitant administration of 40 mg pravastatin had no clinically significant effect on prothrombin time when administered in a study to normal elderly subjects who were stabilized on warfarin.

Cimetidine: The AUC0-12 hr for pravastatin when given with cimetidine was not significantly different from the AUC for pravastatin when given alone. A significant difference was observed between the AUC's for pravastatin when given with cimetidine compared to when administered with antacid.

Digoxin: In a crossover trial involving 18 healthy male subjects given 20 mg pravastatin and 0.2 mg digoxin concurrently for 9 days, the bioavailability parameters of digoxin were not affected. The AUC of pravastatin tended to increase, but the overall bioavailability of pravastatin plus its metabolites SQ 31,906 and SQ 31,945 was not altered.

Cyclosporine: Some investigators have measured cyclosporine levels in patients on pravastatin (up to 20 mg), and to date, these results indicate no clinically meaningful elevations in cyclosporine levels. In one single-dose study, pravastatin levels were found to be increased in cardiac transplant patients receiving cyclosporine.

Gemfibrozil: In a crossover study in 20 healthy male volunteers given concomitant single doses of pravastatin and gemfibrozil, there was a significant decrease in urinary excretion and protein binding of pravastatin. In addition, there was a significant increase in AUC, Cmax, and Tmax for the pravastatin metabolite SQ 31,906. Combination therapy with pravastatin and gemfibrozil is generally not recommended. (See WARNINGS: Skeletal Muscle.)

In interaction studies with aspirin, antacids (1 hour prior to pravastatin sodium), cimetidine, nicotinic acid, or probucol, no statistically significant differences in bioavailability were seen when pravastatin sodium was administered.

Endocrine Function

HMG-CoA reductase inhibitors interfere with cholesterol synthesis and lower circulating cholesterol levels and, as such, might theoretically blunt adrenal or gonadal steroid hormone production. Results of clinical trials with pravastatin in males and post-menopausal females were inconsistent with regard to possible effects of the drug on basal steroid hormone levels. In a study of 21 males, the mean testosterone response to human chorionic gonadotropin was significantly reduced (p<0.004) after 16 weeks of treatment with 40 mg of pravastatin. However, the percentage of patients showing a ≥50% rise in plasma testosterone after human chorionic gonadotropin stimulation did not change significantly after therapy in these patients. The effects of HMG-CoA reductase inhibitors on spermatogenesis and fertility have not been studied in adequate numbers of patients. The effects, if any, of pravastatin on the pituitary-gonadal axis in pre-menopausal females are unknown. Patients treated with pravastatin who display clinical evidence of endocrine dysfunction should be evaluated appropriately. Caution should also be exercised if an HMG-CoA reductase inhibitor or other agent used to lower cholesterol levels is administered to patients also receiving other drugs (e.g., ketoconazole, spironolactone, cimetidine) that may diminish the levels or activity of steroid hormones.

In a placebo-controlled study of 214 pediatric patients with HeFH, of which 106 were treated with pravastatin (20 mg in the children aged 8-13 years and 40 mg in the adolescents aged 14-18 years) for two years, there were no detectable differences seen in any of the endocrine parameters [ACTH, cortisol, DHEAS, FSH, LH, TSH, estradiol (girls) or testosterone (boys)] relative to placebo. There were no detectable differences seen in height and weight changes, testicular volume changes, or Tanner score relative to placebo.

CNS Toxicity

CNS vascular lesions, characterized by perivascular hemorrhage and edema and mononuclear cell infiltration of perivascular spaces, were seen in dogs treated with pravastatin at a dose of 25 mg/kg/day. These effects in dogs were observed at approximately 59 times the human dose of 80 mg/day, based on AUC. Similar CNS vascular lesions have been observed with several other drugs in this class.

A chemically similar drug in this class produced optic nerve degeneration (Wallerian degeneration of retinogeniculate fibers) in clinically normal dogs in a dose-dependent fashion starting at 60 mg/kg/day, a dose that produced mean plasma drug levels about 30 times higher than the mean drug level in humans taking the highest recommended dose (as measured by total enzyme inhibitory activity). This same drug also produced vestibulocochlear Wallerian-like degeneration and retinal ganglion cell chromatolysis in dogs treated for 14 weeks at 180 mg/kg/day, a dose which resulted in a mean plasma drug level similar to that seen with the 60 mg/kg/day dose.

Carcinogenesis, Mutagenesis, Impairment of Fertility

In a 2-year study in rats fed pravastatin at doses of 10, 30, or 100 mg/kg body weight, there was an increased incidence of hepatocellular carcinomas in males at the highest dose (p<0.01). These effects in rats were observed at approximately 12 times the human dose (HD) of 80 mg based on body surface area mg/m^2 and at approximately 4 times the human dose, based on AUC.

In a 2-year study in mice fed pravastatin at doses of 250 and 500 mg/kg/day, there was an increased incidence of hepatocellular carcinomas in males and females at both 250 and 500 mg/kg/day (p<0.0001). At these doses, lung adenomas in females were increased (p=0.013). These effects in mice were observed at approximately 15 times (250 mg/kg/day) and 23 times (500 mg/kg/day) the human dose of 80 mg, based on AUC. In another 2-year study in mice with doses up to 100 mg/kg/day (producing drug exposures approximately 2 times the human dose of 80 mg, based on AUC), there were no drug-induced tumors.

No evidence of mutagenicity was observed in vitro, with or without rat-liver metabolic activation, in the following studies: microbial mutagen tests, using mutant strains of Salmonella typhimurium or Escherichia coli; a forward mutation assay in L5178Y TK +/- mouse lymphoma cells; a chromosomal aberration test in hamster cells; and a gene conversion assay using Saccharomyces cerevisiae. In addition, there was no evidence of mutagenicity in either a dominant lethal test in mice or a micronucleus test in mice.

In a study in rats, with daily doses up to 500 mg/kg, pravastatin did not produce any adverse effects on fertility or general reproductive performance. However, in a study with another HMG-CoA reductase inhibitor, there was decreased fertility in male rats treated for 34 weeks at 25 mg/kg body weight, although this effect was not observed in a subsequent fertility study when this same dose was administered for 11 weeks (the entire cycle of spermatogenesis, including epididymal maturation). In rats treated with this same reductase inhibitor at 180 mg/kg/day, seminiferous tubule degeneration (necrosis and loss of spermatogenic epithelium) was observed. Although not seen with pravastatin, two similar drugs in this class caused drug-related testicular atrophy, decreased spermatogenesis, spermatocytic degeneration, and giant cell formation in dogs. The clinical significance of these findings is unclear.

Pregnancy

Pregnancy Category X.

See CONTRAINDICATIONS.

Safety in pregnant women has not been established. Pravastatin was not teratogenic in rats at doses up to 1000 mg/kg daily or in rabbits at doses of up to 50 mg/kg daily. These doses resulted in 10X (rabbit) or 120X (rat) the human exposure based on surface area (mg/meter^2). Rare reports of congenital anomalies have been received following intrauterine exposure to other HMG-CoA reductase inhibitors. In a review^7 of approximately 100 prospectively followed pregnancies in women exposed to simvastatin or lovastatin, the incidences of congenital anomalies, spontaneous abortions and fetal deaths/stillbirths did not exceed what would be expected in the general population. The number of cases is adequate only to exclude a three-to-four-fold increase in congenital anomalies over the background incidence. In 89% of the prospectively followed pregnancies, drug treatment was initiated prior to pregnancy and was discontinued at some point in the first trimester when pregnancy was identified. As safety in pregnant women has not been established and there is no apparent benefit to therapy with pravastatin sodium during pregnancy (see CONTRAINDICATIONS), treatment should be immediately discontinued as soon as pregnancy is recognized. Pravastatin sodium should be administered to women of child-bearing potential only when such patients are highly unlikely to conceive and have been informed of the potential hazards.

Nursing Mothers

A small amount of pravastatin is excreted in human breast milk. Because of the potential for serious adverse reactions in nursing infants, women taking pravastatin sodium should not nurse (see CONTRAINDICATIONS).

Pediatric Use

The safety and effectiveness of pravastatin sodium in children and adolescents from 8-18 years of age have been evaluated in a placebo-controlled study of 2 years duration. Patients treated with pravastatin had an adverse experience profile generally similar to that of patients treated with placebo with influenza and headache commonly reported in both treatment groups. (See ADVERSE REACTIONS: Pediatric Patients.) Doses greater than 40 mg have not been studied in this population. Children and adolescent females of childbearing potential should be counseled on appropriate contraceptive methods while on pravastatin therapy (see CONTRAINDICATIONSand PRECAUTIONS: Pregnancy). For dosing information see DOSAGE AND ADMINISTRATION: Adult Patients andPediatric Patients.

Double-blind, placebo-controlled pravastatin studies in children less than 8 years of age have not been conducted.

Geriatric Use

The beneficial effect of pravastatin in elderly subjects in reducing cardiovascular events and in modifying lipid profiles was similar to that seen in younger subjects. The adverse event profile in the elderly was similar to that in the overall population. Other reported clinical experience has not identified differences in responses to pravastatin between elderly and younger patients.

Mean pravastatin AUCs are slightly (25-50%) higher in elderly subjects than in healthy young subjects, but mean Cmax, Tmax and t½ values are similar in both age groups and substantial accumulation of pravastatin would not be expected in the elderly (see CLINICAL PHARMACOLOGY: Pharmacokinetics/Metabolism).

ADVERSE REACTIONS

Pravastatin is generally well tolerated; adverse reactions have usually been mild and transient. In 4-month-long placebo-controlled trials, 1.7% of pravastatin-treated patients and 1.2% of placebo-treated patients were discontinued from treatment because of adverse experiences attributed to study drug therapy; this difference was not statistically significant. (See also PRECAUTIONS: Geriatric Use.)

Adverse Clinical Events

Short-Term Controlled Trials

All adverse clinical events (regardless of attribution) reported in more than 2% of pravastatin-treated patients in placebo-controlled trials of up to four months duration are identified in Table 6; also shown are the percentages of patients in whom these medical events were believed to be related or possibly related to the drug:

Table 6: Adverse Events in >2 Percent of Patients Treated with Pravastatin 10-40 mg in Short-Term Placebo-Controlled Trials
 | All Events |  | Events Attributed to Study Drug
Body System/Event | Pravastatin (N=900) % of patients | Placebo (N=411) % of patients | Pravastatin (N=900) % of patients | Placebo (N=411) % of patients
Cardiovascular Cardiac Chest Pain | 4.0 | 3.4 | 0.1 | 0.0
Dermatologic Rash | 4.0* | 1.1 | 1.3 | 0.9
Gastrointestinal Nausea/Vomiting Diarrhea Abdominal Pain Constipation Flatulence Heartburn | 7.3 6.2 5.4 4.0 3.3 2.9 | 7.1 5.6 6.9 7.1 3.6 1.9 | 2.9 2.0 2.0 2.4 2.7 2.0 | 3.4 1.9 3.9 5.1 3.4 0.7
General Fatigue Chest Pain Influenza | 3.8 3.7 2.4* | 3.4 1.9 0.7 | 1.9 0.3 0.0 | 1.0 0.2 0.0
Musculoskeletal Localized Pain Myalgia | 10.0 2.7 | 9.0 1.0 | 1.4 0.6 | 1.5 0.0
Nervous System Headache Dizziness | 6.2 3.3 | 3.9 3.2 | 1.7* 1.0 | 0.2 0.5
Renal/Genitourinary Urinary Abnormality | 2.4 | 2.9 | 0.7 | 1.2
Respiratory Common Cold Rhinitis Cough | 7.0 4.0 2.6 | 6.3 4.1 1.7 | 0.0 0.1 0.1 | 0.0 0.0 0.0
*Statistically significantly different from placebo.

The safety and tolerability of pravastatin at a dose of 80 mg in two controlled trials with a mean exposure of 8.6 months was similar to that of pravastatin at lower doses except that 4 out of 464 patients taking 80 mg of pravastatin had a single elevation of CK >10X ULN compared to 0 out of 115 patients taking 40 mg of pravastatin.

Long-Term Controlled Morbidity and Mortality Trials

Adverse event data were pooled from seven double-blind, placebo-controlled trials (West of Scotland Coronary Prevention Study [WOS]; Limitation of Atherosclerosis in the Coronary Arteries study [PLAC I]; Pravastatin, Lipids and Atherosclerosis in the Carotids study [PLAC II]; Regression Growth Evaluation Statin Study [REGRESS]; and Kuopio Atherosclerosis Prevention Study [KAPS]) involving a total of 10,764 patients treated with pravastatin 40 mg and 10,719 patients treated with placebo. The safety and tolerability profile in the pravastatin group was comparable to that of the placebo group. Patients were exposed to pravastatin for a mean of 4.0 to 5.1 years in WOS and 1.9 to 2.9 years in PLAC I, PLAC II, KAPS, and REGRESS. In these long-term trials, the most common reasons for discontinuation were mild, non-specific gastrointestinal complaints. Collectively, these seven trials represent 47,613 patient-years of exposure to pravastatin. Events believed to be of probable, possible, or uncertain relationship to study drug, occurring in at least 1% of patients treated with pravastatin in these studies are identified in Table 7.

Table 7: Adverse Events in ≥1 Percent of Patients Treated with Pravastatin 40 mg in Long-Term Placebo-Controlled Trials
Body System/Event | Pravastatin (N=10,764) % of patients | Placebo (N=10,719) % of patients
Cardiovascular Angina Pectoris | 3.1 | 3.4
Dermatologic Rash | 2.1 | 2.2
Gastrointestinal Dyspepsia/Heartburn Abdominal Pain Nausea/Vomiting Flatulence Constipation | 3.5 2.4 1.6 1.2 1.2 | 3.7 2.5 1.6 1.1 1.3
General Fatigue Chest Pain | 3.4 2.6 | 3.3 2.6
Musculoskeletal Musculoskeletal Pain (includes arthralgia) Muscle Cramp Myalgia | 6.0 2.0 1.4 | 5.8 1.8 1.4
Nervous System Dizziness Headache Sleep Disturbance Depression Anxiety/Nervousness | 2.2 1.9 1.0 1.0 1.0 | 2.1 1.8 0.9 1.0 1.2
Renal/Genitourinary Urinary Abnormality (includes dysuria, frequency, nocturia) | 1.0 | 0.8
Respiratory Dyspnea Upper Respiratory Infection Cough | 1.6 1.3 1.0 | 1.6 1.3 1.0
Special Senses Vision Disturbance (includes blurred vision, diplopia) | 1.6 | 1.3

Events of probable, possible, or uncertain relationship to study drug that occurred in <1.0% of pravastatin-treated patients in the long-term trials included the following; frequencies were similar in placebo-treated patients:

Dermatologic: pruritus, dermatitis, dryness skin, scalp hair abnormality (including alopecia), urticaria.

Endocrine/Metabolic: sexual dysfunction, libido change.

Gastrointestinal: decreased appetite.

General: fever, flushing.

Immunologic: allergy, edema head/neck.

Musculoskeletal: muscle weakness.

Nervous System: paresthesia, vertigo, insomnia, memory impairment, tremor, neuropathy (including peripheral neuropathy).

Special Senses: lens opacity, taste disturbance.

Postmarketing Experience

In addition to the events reported above, as with other drugs in this class, the following events have been reported rarely during postmarketing experience with pravastatin sodium tablets, regardless of causality assessment:

Musculoskeletal: myopathy, rhabdomyolysis.

Nervous System: dysfunction of certain cranial nerves (including alteration of taste, impairment of extraocular movement, facial paresis), peripheral nerve palsy.

Hypersensitivity: anaphylaxis, angioedema, lupus erythematosus-like syndrome, polymyalgia rheumatica, dermatomyositis, vasculitis, purpura, hemolytic anemia, positive ANA, ESR increase, arthritis, arthralgia, asthenia, photosensitivity, chills, malaise, toxic epidermal necrolysis, erythema multiforme, including Stevens-Johnson syndrome.

Gastrointestinal: pancreatitis, hepatitis, including chronic active hepatitis, cholestatic jaundice, fatty change in liver, cirrhosis, fulminant hepatic necrosis, hepatoma.

Dermatologic: a variety of skin changes (e.g., nodules, discoloration, dryness of mucous membranes, changes to hair/nails).

Reproductive: gynecomastia.

Laboratory Abnormalities: LFTabnormalities, thyroid function abnormalities.

Laboratory Test Abnormalities

Increases in serum transaminase (ALT, AST) values and CPK have been observed (see WARNINGS).

Transient, asymptomatic eosinophilia has been reported. Eosinophil counts usually returned to normal despite continued therapy. Anemia, thrombocytopenia, and leukopenia have been reported with HMG-CoA reductase inhibitors.

Concomitant Therapy

Pravastatin has been administered concurrently with cholestyramine, colestipol, nicotinic acid, probucol and gemfibrozil. Preliminary data suggest that the addition of either probucol or gemfibrozil to therapy with lovastatin or pravastatin is not associated with greater reduction in LDL-cholesterol than that achieved with lovastatin or pravastatin alone. No adverse reactions unique to the combination or in addition to those previously reported for each drug alone have been reported. Myopathy and rhabdomyolysis (with or without acute renal failure) have been reported when another HMG-CoA reductase inhibitor was used in combination with immunosuppressive drugs, gemfibrozil, erythromycin, or lipid-lowering doses of nicotinic acid. Concomitant therapy with HMG-CoA reductase inhibitors and these agents is generally not recommended. (See WARNINGS: Skeletal Muscle and PRECAUTIONS: Drug Interactions.)

Pediatric Patients

In a two (2) year, double-blind, placebo-controlled study involving 100 boys and 114 girls with HeFH, the safety and tolerability profile of pravastatin was generally similar to that of placebo. (See CLINICAL PHARMACOLOGY: Pediatric Clinical Study and PRECAUTIONS: Pediatric Use.)

OVERDOSAGE

To date, there has been limited experience with overdosage of pravastatin. If an overdose occurs, it should be treated symptomatically with laboratory monitoring and supportive measures should be instituted as required. (See WARNINGS.)

DOSAGE AND ADMINISTRATION

The patient should be placed on a standard cholesterol-lowering diet before receiving pravastatin sodium tablets and should continue on this diet during treatment with pravastatin sodium tablets (see NCEP Treatment Guidelines for details on dietary therapy).

Pravastatin sodium tablets can be administered orally as a single dose at any time of the day, with or without food. Since the maximal effect of a given dose is seen within 4 weeks, periodic lipid determinations should be performed at this time and dosage adjusted according to the patient's response to therapy and established treatment guidelines.

Adult Patients

The recommended starting dose is 40 mg once daily. If a daily dose of 40 mg does not achieve desired cholesterol levels, 80 mg once daily is recommended. In patients with a history of significant renal or hepatic dysfunction, a starting dose of 10 mg daily is recommended.

Pediatric Patients

Children (Ages 8 to 13 Years, Inclusive)

The recommended dose is 20 mg once daily in children 8 to 13 years of age. Doses greater than 20 mg have not been studied in this patient population.

Adolescents (Ages 14 to 18 Years)

The recommended starting dose is 40 mg once daily in adolescents 14 to 18 years of age. Doses greater than 40 mg have not been studied in this patient population.

Children and adolescents treated with pravastatin should be re-evaluated in adulthood and appropriate changes made to their cholesterol-lowering regimen to achieve adult goals for LDL-C (see INDICATIONS AND USAGE: Hyperlipidemia, NCEP Treatment Guidelines).

In patients taking immunosuppressive drugs such as cyclosporine (see WARNINGS: Skeletal Muscle) concomitantly with pravastatin, therapy should begin with 10 mg of pravastatin once-a-day at bedtime and titration to higher doses should be done with caution. Most patients treated with this combination received a maximum pravastatin dose of 20 mg/day.

Concomitant Therapy

The lipid-lowering effects of pravastatin sodium on total and LDL cholesterol are enhanced when combined with a bile-acid-binding resin. When administering a bile-acid-binding resin (e.g., cholestyramine, colestipol) and pravastatin, pravastatin sodium tablets should be given either 1 hour or more before or at least 4 hours following the resin. (See also ADVERSE REACTIONS: Concomitant Therapy.)

HOW SUPPLIED

Pravastatin Sodium Tablets, USP 10 mg are available for oral administration as light pink, round, unscored tablets, imprinted “APO” on one side and “PRA” over “10” on the other side. They are supplied as follows:

NDC: 35356-921-30 Bottles of 30

NDC: 35356-921-60 Bottles of 60

NDC: 35356-921-90 Bottles of 90

Pravastatin Sodium Tablets, USP 20 mg are available for oral administration as off-white to light yellow, round, unscored tablets, imprinted “APO” on one side and “PRA” over “20” on the other side. They are supplied as follows:

NDC: 35356-919-30 Bottles of 30

NDC: 35356-919-60 Bottles of 60

NDC: 35356-919-90 Bottles of 90

Pravastatin Sodium Tablets, USP 40 mg are available for oral administration as light green, round, unscored tablets, imprinted “APO” on one side and “PRA” over “40” on the other side. They are supplied as follows:

NDC: 35356-125-30 Bottles of 30

NDC: 35356-125-60 Bottles of 60

NDC: 35356-125-90 Bottles of 90

Pravastatin Sodium Tablets, USP 80 mg are available for oral administration as off-white to light yellow, round, unscored tablets, imprinted "APO" on one side and "PRA" over "80" on the other side. They are supplied as follows:

Storage

Store at 20° to 25°C (68° to 77°F); excursions permitted to 15° to 30°C (59° to 86°F). [see USP Controlled Room Temperature]. Dispense in a tight, light-resistant container [see USP].

Protect from light and moisture.

REFERENCES

1. Shepherd J, et al. Prevention of Coronary Heart Disease with Pravastatin in Men with Hypercholesterolemia (WOS). N Engl J Med 1995; 333:1301-7.
2. Pitt B, et al. Pravastatin Limitation of Atherosclerosis in the Coronary Arteries (PLAC I): Reduction in Atherosclerosis Progression and Clinical Events. J Am Coll Cardiol 1995; 26:1133-9.
3. Jukema JW, et al. Effects of Lipid Lowering by Pravastatin on Progression and Regression of Coronary Artery Disease in Symptomatic Man with Normal to Moderately Elevated Serum Cholesterol Levels. The Regression Growth Evaluation Statin Study (REGRESS). Circulation 1995; 91:2528-2540.
4. Crouse JR, et al. Pravastatin, Lipids, and Atherosclerosis in the Carotid Arteries: Design Features of a Clinical Trial with Carotid Atherosclerosis Outcome (PLAC II). Controlled Clinical Trials 1992; 13:495.
5. Salonen R, et al. Kuopio Atherosclerosis Prevention Study (KAPS). A Population-based Primary Preventive Trial of the Effect of LDL Lowering on Atherosclerotic Progression in Carotid and Femoral Arteries. Research Institute of Public Health, University of Kuopio, Finland. Circulation 1995; 92:1758.
6. Fredrickson DS, et al. Fat Transport in Lipoproteins-An Integrated Approach to Mechanisms and Disorders. N Engl J Med 1967; 276:34-42, 94-102, 148-156, 215-224, 273-281.
7. Manson JM, Freyssinges C, Ducrocq MB, Stephenson WP. Postmarketing Surveillance of Lovastatin and Simvastatin Exposure During Pregnancy. Reproductive Toxicology 1996; 10(6): 439-446.

APOTEX INC. PRAVASTATIN SODIUM TABLETS, USP
10 mg, 20 mg, 40 mg and 80 mg

Manufactured by: | Manufactured for:
Apotex Inc. | Apotex Corp.
Toronto, Ontario | Weston, Florida
Canada M9L 1T9 | 33326

Revised: February 2011

Rev. 7